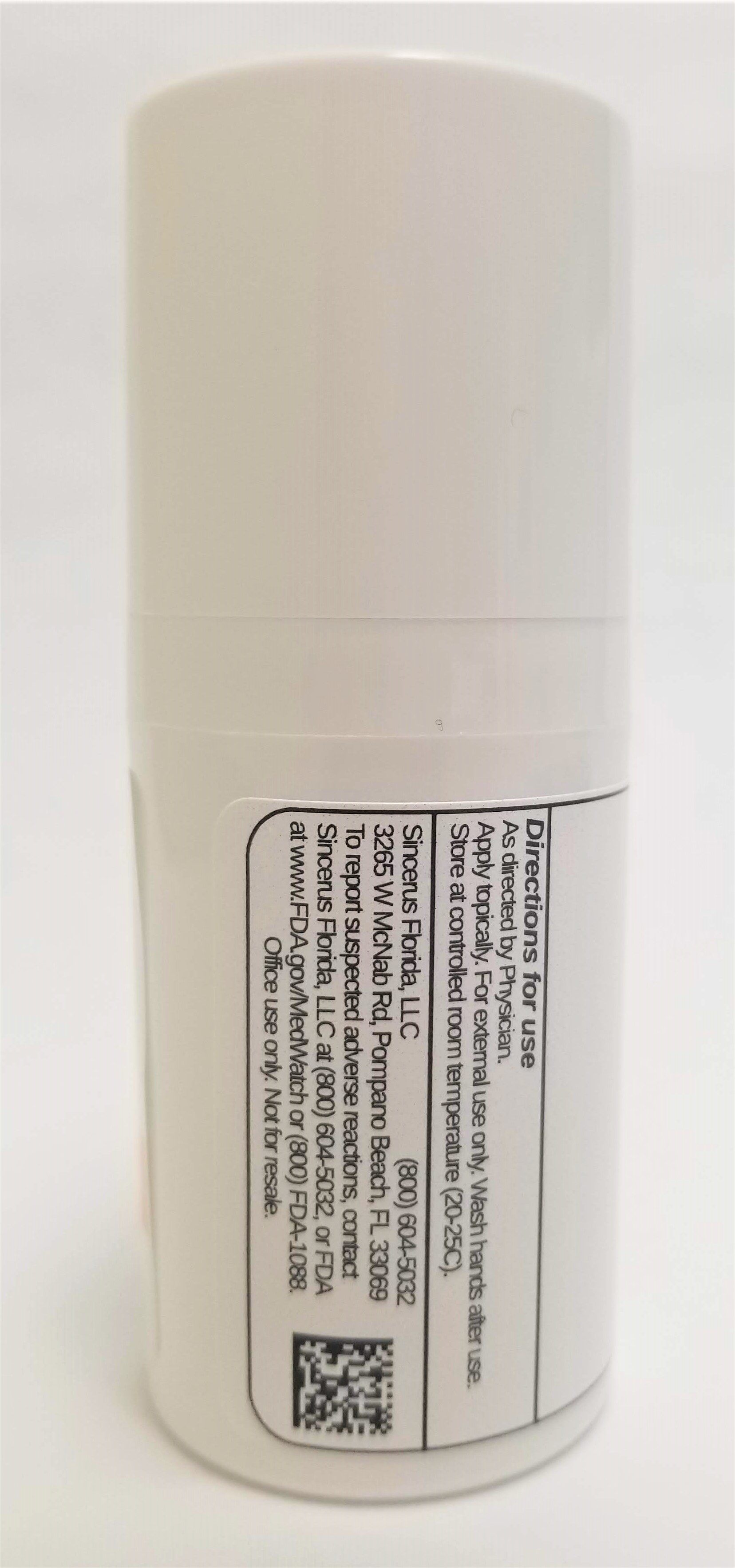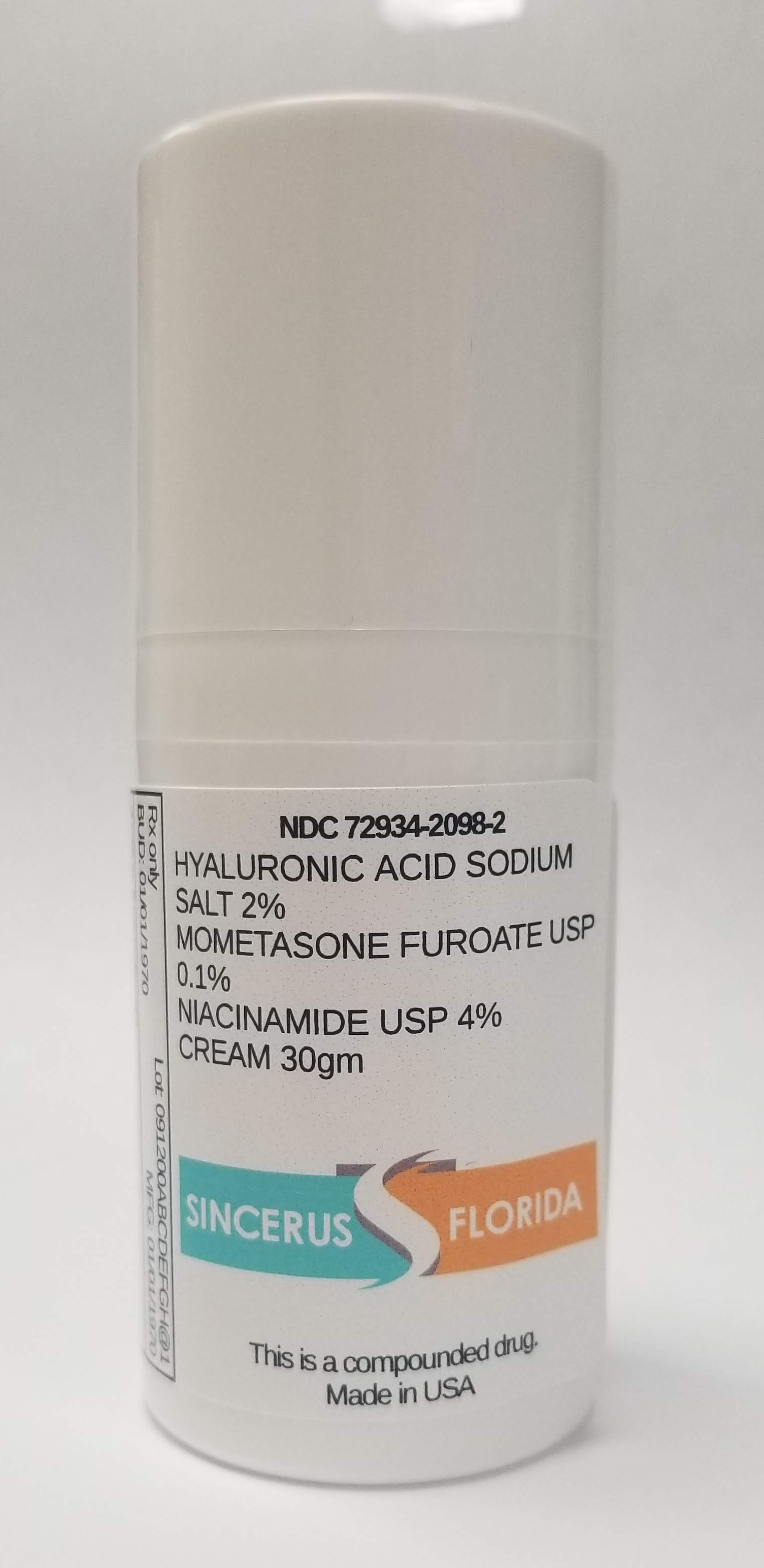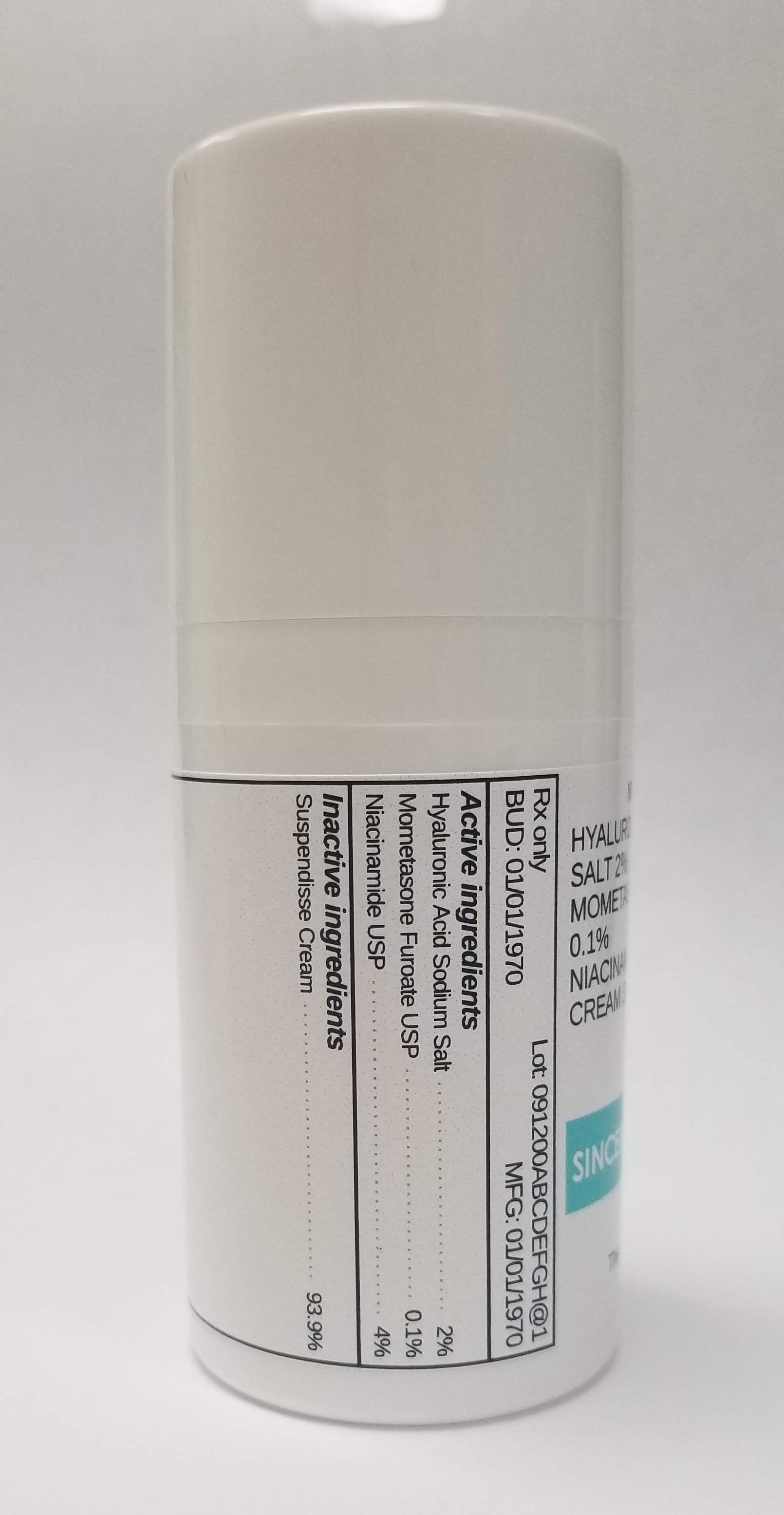 DRUG LABEL: HYALURONIC ACID SODIUM SALT 2% / MOMETASONE FUROATE 0.1% / NIACINAMIDE 4%
NDC: 72934-2098 | Form: CREAM
Manufacturer: Sincerus Florida, LLC
Category: prescription | Type: HUMAN PRESCRIPTION DRUG LABEL
Date: 20190521

ACTIVE INGREDIENTS: HYALURONIC ACID 2 g/100 g; MOMETASONE FUROATE 0.1 g/100 g; NIACINAMIDE 4 g/100 g

HYALURONIC ACID SODIUM SALT 2% / MOMETASONE FUROATE 0.1% / NIACINAMIDE 4%